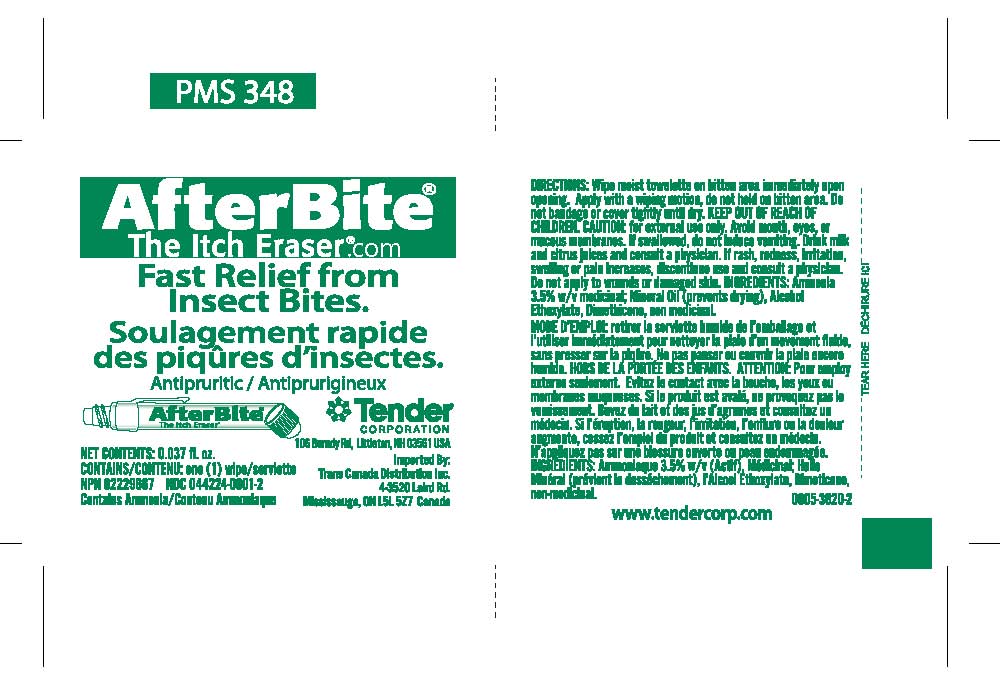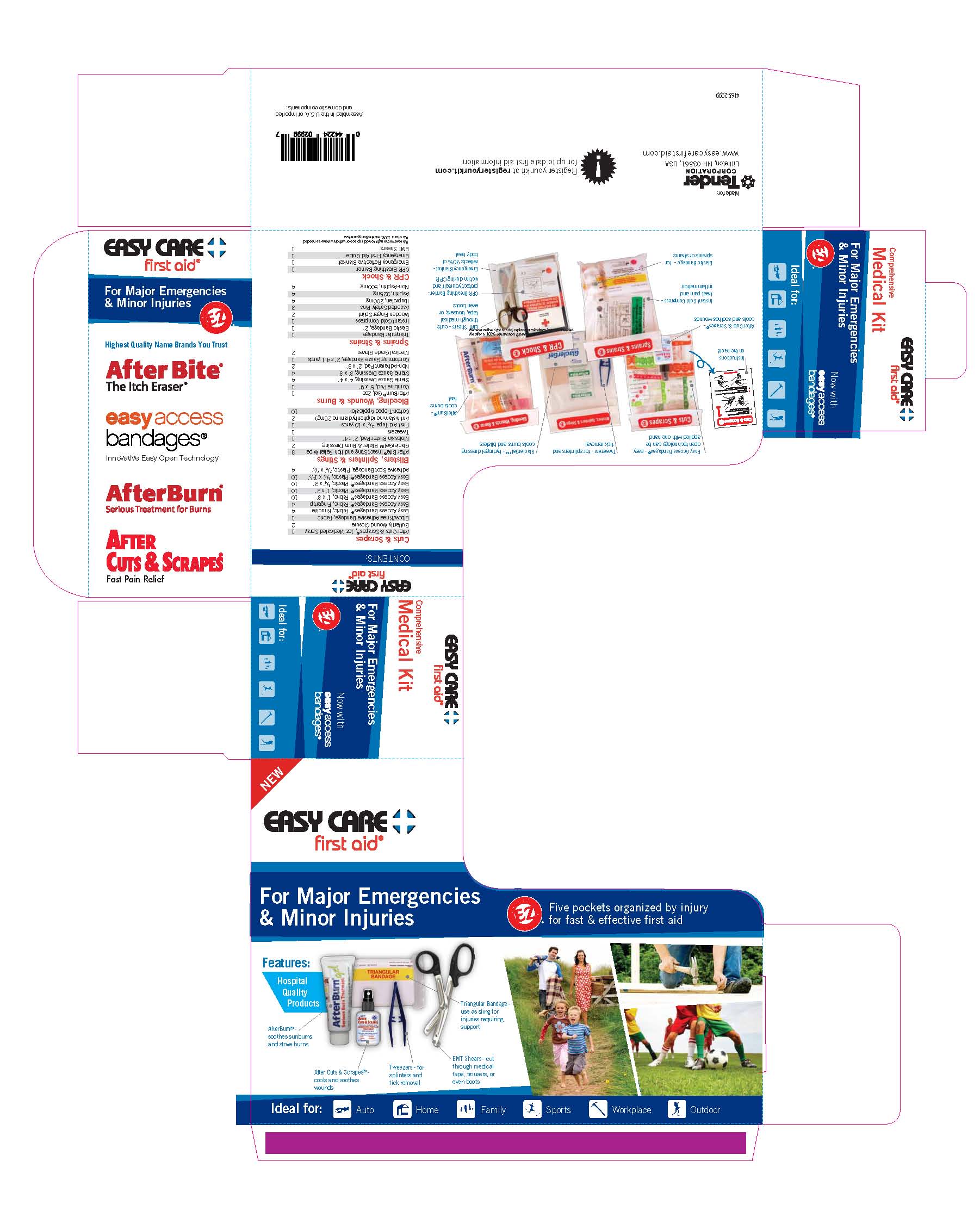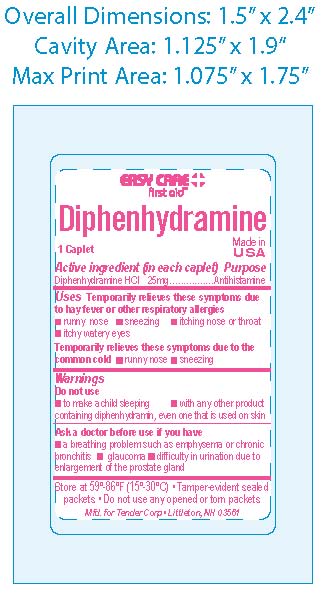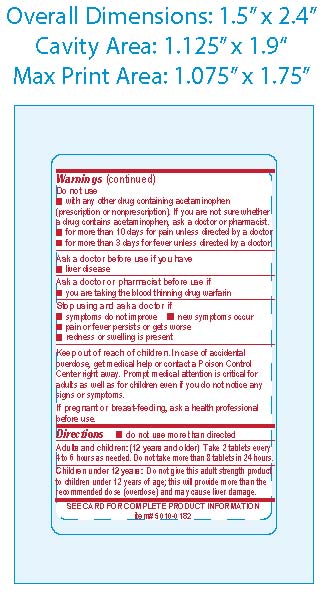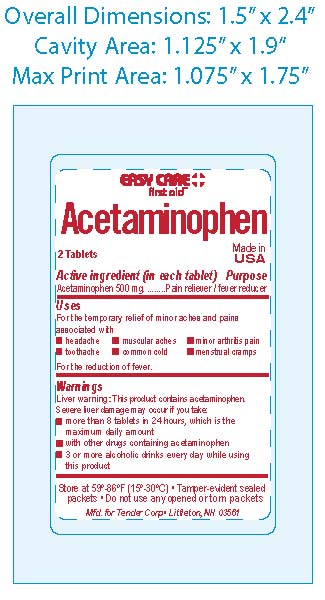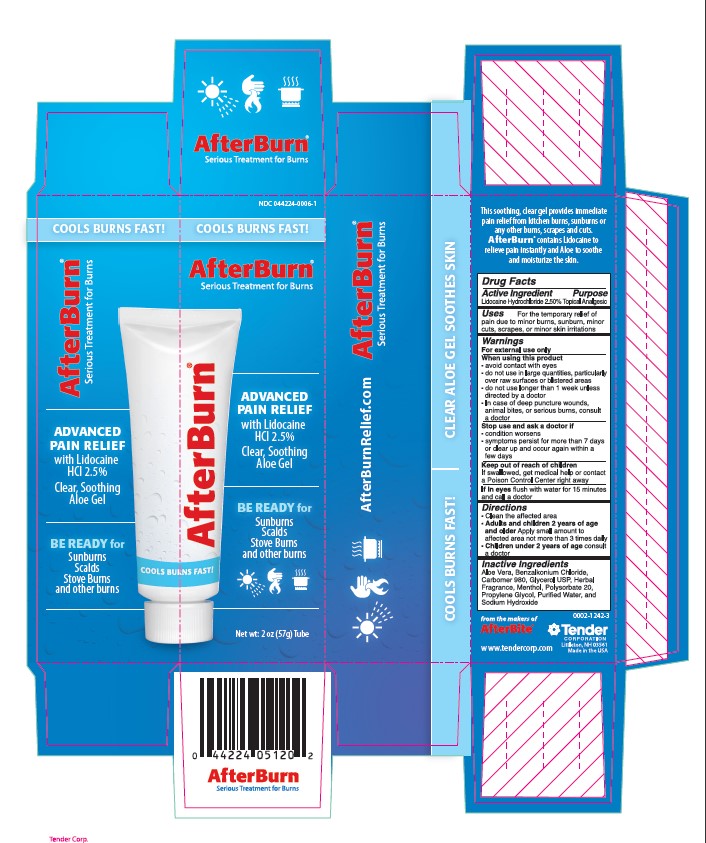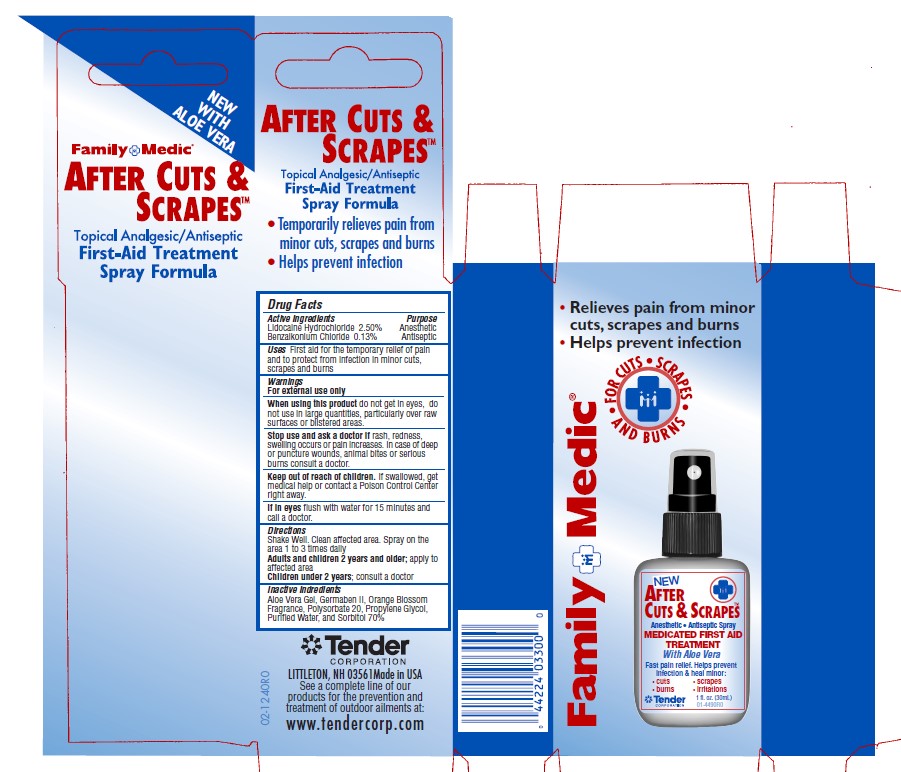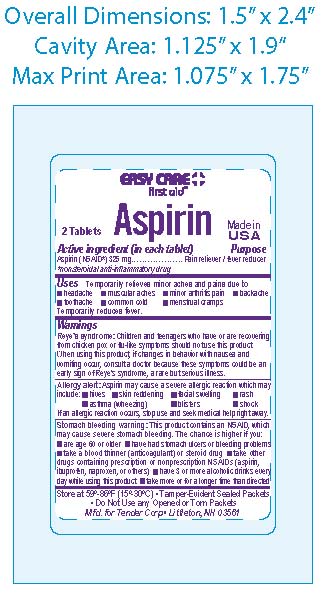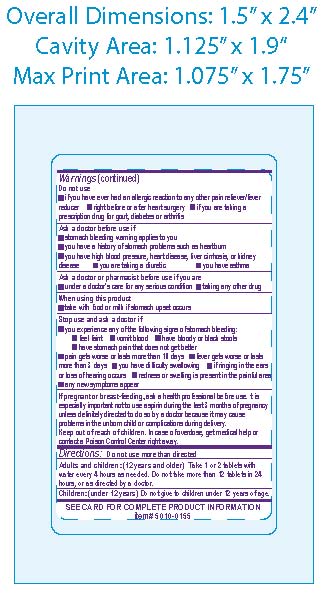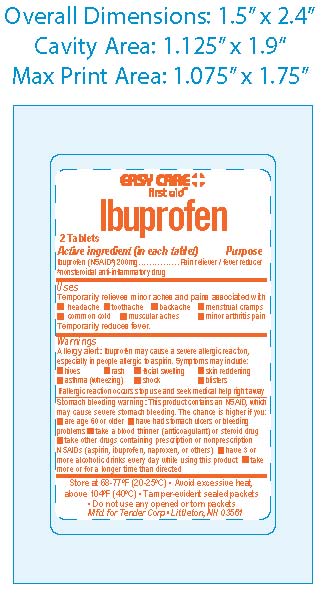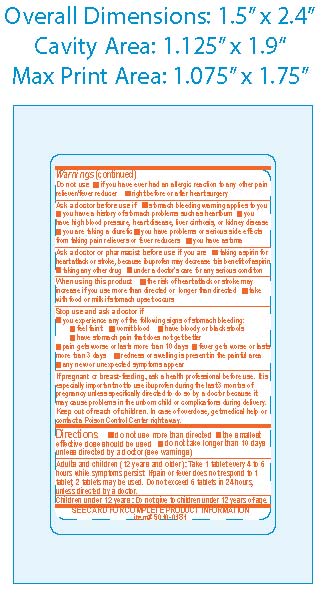 DRUG LABEL: Easy Care First Aid Kit - Comprehensive
NDC: 44224-2999 | Form: KIT | Route: TOPICAL
Manufacturer: Tender Corporation
Category: otc | Type: HUMAN OTC DRUG LABEL
Date: 20170309

ACTIVE INGREDIENTS: LIDOCAINE HYDROCHLORIDE 25 mg/1 mL; IBUPROFEN 200 mg/1 1; ASPIRIN 325 mg/1 1; DIPHENHYDRAMINE HYDROCHLORIDE 25 mg/1 1; BENZALKONIUM CHLORIDE 26 mg/1 mL; LIDOCAINE HYDROCHLORIDE 25 mg/1 mL; ACETAMINOPHEN 500 mg/1 1; AMMONIA 30 mg/1 mL
INACTIVE INGREDIENTS: CARBOMER HOMOPOLYMER TYPE C; SODIUM HYDROXIDE; ALOE VERA LEAF; BENZALKONIUM CHLORIDE; GLYCERIN; MENTHOL; SILICON DIOXIDE; FERRIC OXIDE RED; SODIUM STARCH GLYCOLATE TYPE A POTATO; POLYVINYL ALCOHOL, UNSPECIFIED; TALC; POLYETHYLENE GLYCOLS; STEARIC ACID; STARCH, CORN; TITANIUM DIOXIDE; CELLULOSE, MICROCRYSTALLINE; CROSCARMELLOSE SODIUM; TITANIUM DIOXIDE; MINERAL OIL; HYPROMELLOSES; STARCH, CORN; CELLULOSE, MICROCRYSTALLINE; D&C RED NO. 27; POLYETHYLENE GLYCOLS; TITANIUM DIOXIDE; CARNAUBA WAX; CROSCARMELLOSE SODIUM; DIBASIC CALCIUM PHOSPHATE DIHYDRATE; HYPROMELLOSES; MAGNESIUM STEARATE; POLYSORBATE 80; SILICON DIOXIDE; PROPYLENE GLYCOL; DIAZOLIDINYL UREA; POLYSORBATE 20; SORBITOL; ALOE VERA LEAF; WATER; HYPROMELLOSES; POLYETHYLENE GLYCOLS; CELLULOSE, MICROCRYSTALLINE; MALTODEXTRIN; POVIDONE; SODIUM STARCH GLYCOLATE TYPE A POTATO; STARCH, CORN; STEARIC ACID; WATER; LIGHT MINERAL OIL; DIMETHICONE 1000; C12-13 ALCOHOLS

Easy Care Comprehensive First Aid Kit

Active Ingredients - After Bite Wipe

Ammonia 3.5%

Purpose - After Bite Wipe

Counterirritant

Use - After Bite Wipe

Temporarily protects and helps relieve minor skin irritation and itching due to - insect bites and stings, poison ivy, oak or sumac

Warnings - After Bite Wipes

For External Use Only

Keep Out of Reach of Children - After Bite

Keep out of reach of children: if swallowed, get medical help or contact a Poison Control Center right away

Stop Use - After Bite Wipe

Stop use and ask a doctor if: Condition worsens, symptoms last more than 7 days or clear up and occur again within a few days

When Using - After Bite

Do not get into eyes

Directions - After Bite Wipe

Adults and Children 2 years and older - dab directly on bite or sting, rub gently and reapply as needed

Children under 2 years - ask a doctor

Active Ingredient - Aspirin

Aspirin (NSAID*) 325mg *nonsteroidal anti-inflammatory drug

Purpose - Aspirin

Pain Reliever/Fever Reducer

When Using - Aspirin

Reye's Syndrome: Children and teenagers who have or are recovering from chicken pox or Flu-like symptoms should not use this product. When using this product, if changes in behavior with nausea and vomiting occur, consult a doctor because these symptoms could be an early sign of Reye's syndrome, a rare but serious illness.

Allergy Alert: Aspirin may cause a severe allergic reaction which may include: hives, skin reddening, facial swelling, rash, asthma (wheezing), blisters or shock. If an allergic reaction occurs, stop use and seek medical help right away.

Stomach bleeding warning: this contains an NSAID, which may cause severe stomach bleeding. The chance is higher if you: are age 60 or older; have had stomach ulcers or bleeding problems, take a blood thinner (anticoagulant) or steroid drug; take other drugs containing prescription or nonprescription NSAIDs (aspirin, ibuprofen, naproxen or others), have 3 or more alcoholic drinks everyday while using this problem, take more for a longer time than directed.

Do not use if you have ever had an allergic reaction to any other pain reliever/fever reducer; right before or after heart surgery, if you are taking a prescription drug for gout, diabetes or arthritis.

Ask a doctor before use if: stomach bleeding warning applies to you, you have a history of stomach problems such as heartburn, you have high blood pressure, heart disease, liver cirrhosis or kidney disease, you are taking a diuretic.

Ask a Doctor or Pharmacist before use if you are: under a doctor's care for any serious condition, taking any other drug.

When using this product: take with food or milk if stomach upset occurs

Stop use and Ask a Doctor if: you experience any of the following signs of stomach bleeding, you feel faint, vomit blood, have bloody or black stools, have stomach pain that does not get better, gets worse or lasts more than 10 days, fever gets worse or lasts more than 3 days, you have difficulty swallowing, if ringing in the ears or loss of hearing occurs, redness or swelling is present in painful areas, or any new symptoms appear.

If pregnant or Breastfeeding, ask a health professional before use. It is especially important not to use aspirin during the last 3 months of pregnancy unless directed to do so by a doctor because it may cause problems in the unborn child or complications during deliver.

Keep out of reach of Children. In case of overdose, get medical help or contact a poison control center right away.

Directions - Aspirin

Do not use more than directed - the smallest effective dosage should be used. Drink a full glass of water with each dose. Do not take longer than 10 days, unless directed by a doctor.

Adults and Children (12 years and older): take 1 or 2 tablets with water every 4 hours as needed. Do not take more than 12 tablets in 24 hours or as directed as a doctor.

Children under 12 years: Do not give to children under 12 years of age

Avoid excessive heat and humidity, do not use any open or torn packets.

Use - Aspirin

Temporariy relieves minor aches and pains associated with: headache, muscular aches, minor arthritis pain, backache, common cold, toothache, menstrual cramps, temorarily reduces fever.

Active Ingredient - Ibuprofen

Ibuprofen

Purpose - Ibuprofen

Pain Reliever/Fever Reducer

Use - Ibuprofen

Temporarily relieves minor aches and pains due to: the common cold, headache, toothache, muscular aches, backache, minor pain of arthritis, menstrual cramps. Temporarily reduces fever.

Warnings and Precautions - Ibuprofen

Allergy alert: ibuprofen may cause a severe allergic reaction, especially in people allergic to aspirin. Symptoms may include: shock, facial swelling, asthma (wheezing), rash, skin reddening, blisters, and hives, if an allergic reaction occurs, stop use and seek medical help right away.

Stomach bleeding warning: this product contains a nonsteroidal anti-inflammatory drug (NSAID), which may cause severe stomach bleeding. The chance is higher if you: are age 60 or older, have had stomach ulcers or bleeding problems, take a blood thinner (anticoagulant) or steroid drug, take other drugs containing NSAIDs (aspirin, ibuprofen, naproxen or others), have 3 or more alcoholic drinks every day while using this product, take more or for a longer time than directed.

Do not use if you have ever had an allergic reaction to any other pain reliever/fever reducer, fight before or after heart surgery.

Ask a doctor before use if stomach bleeding warning applies to you, you have had a history of stomach problems such as heartburn, you have a high blood pressure, heart disease, liver cirrhosis, or kidney disease, you are taking a diuretic.

Ask a doctor before use if you are taking any other drug containing NSAID (prescription or nonprescription), taking aspirin for heart attack or stroke, because Ibuprofen may decrease this benefit of aspirin, taking any other drug.

When using this product take with food or milk if stomach upset occurs.

Stop use and ask a doctor if you experience any of the following signs of stomach bleeding, feeling faint, vomit blood, have bloody or black stools, have stomach pain that does not get better, pain gets worse or lasts more than 10 days, fever gets worse or lasts more than 3 days, redness or swelling is present in the painful area, any new symptoms appear.

If pregnant or breast-feeding, ask a health professional before use. It is especially important not to use ibuprofen during the last 3 months of pregnancy unless definitely directed to do so by a doctor because it may cause problems in the unborn child or complications during delivery.

Keep out of reach of children. In case of overdose, get medical help or contact a poison control center right away.

Store at controlled room temperature, avoid excessive heat 40 degrees Celsius (104 degrees Fahrenheit); temper evident sealed packets, do not use any opened or torn packets.

Do not use more than directed, the smallest effective dose should be used, do not take longer than 10 days, unless directed by a doctor. Adults and Children (12 years and older): take 1 tablet every 4 to 6 hours while symptoms persist. If pain or fever does not respond to 1 tablet, 3 tablets may be use. Do not exceed 6 tablets in 24 hours, unless directed by a doctor. Children under 12 years: do not give children under 12 years of age.

Active Ingredient - APAP

Acetaminophen 500mg

Purpose - APAP

Analgesic/antipyretic

Uses - APAP

Temporary relief of minor aches and pains associated with: common cold, headache, toothache, muscular aches, backache, arthritis, menstrual cramps, and reduction of fever

Warnings and Precautions - APAP

Liver Warning: This product contains acetaminophen.

Severe liver damage may occur if: adult takes more than 12 tablets in 24 hours, which is the maximum daily amount, child takes more than 5 doses in 24 hours, taken with other drugs containing acetaminophen, adult has 3 or more alcoholic drinks ever day while using this product.

Do not use with any other drug containing acetaminophen (prescription or nonprescription). If you are not sure whether a drug contains acetaminophen, ask a doctor or pharmacist, for more than 10 days for pain unless directed by a doctor, for more than 3 days for fever unless directed by a doctor.

Ask a doctor before use if the user has liver disease.

Ask a doctor or pharmacist before use if the user is taking the blood thinning drug warfarin.

Stop use and ask a doctor if: symptoms do not improve, pain gets worse or lasts more than 10 days, fever gets worse or lasts more than 3 days, new symptoms occur, redness or swelling is present, a rare sensitivity reaction occurs.

If pregnant or breast-feeding, ask a health professional before use.

Keep out of reach of children. In case of accidental overdose, contact a doctor or Poison Control Center immediately. Prompt medical attention is critical for adults as well for children even if you do not notice any signs or symptoms. Do not exceed recommended dosage.

Store at 59-86 degrees F (15-30 degrees C), tamper evident sealed packets, do not use any open or torn packets.

Directions - APAP

Adult and Children (12 years and older) take 2 tablets every 4 to 6 hours as needed. Do not take more than 12 tablets in 24 hours.

Children 6-11 years take 1 tablet every 4 to 6 hours as needed. Do not take more than 5 tablets in 24 hours.

Childen under 6 do not use this product

Active Ingredient - Diphenhydramine

Diphenhydramine Hydrochloride 25mg

Purpose - Diphenhydramine

Antihistamine

Use - Diphenhydramine

Temporarily relieves these symptoms due to hay fever or other respiratory allergies: runny nose, sneezing, itching nose or throat, itchy-watery eyes.

Temporarily relieves these symptoms due to the common cold: runny nose, sneezing

Warnings and Precautions - Diphenhydramine

Do not use to make a child sleepy or with any other product containing diphenhydramine, even one that is used on skin.

Ask a doctor before use if you have: a breathing problem such as emphysema or chronic bronchitis, difficulty in urination due to enlargement of the prostate gland, or glaucoma.

Ask a doctor pharmacist before you use if you are taking sedatives or tranquilizers.

When using this product: marked drowsiness may occur, avoid alcoholic beverages, alcohol, sedatives and tranquilizers may increase the drowsiness effect, use caution when driving a motor vehicle or operating machinery, excitability may occur, especially in children.

If pregnant or breast feeding, ask a health professional before use.

Keep out of reach of Children. In case of overdose, contact a physician or poison control center immediately.

Each caplet may contain calcium 25mg. Store at room temperature 59-86 degrees F (15-30 C), protect from light and use by expiration date on packet. Tamper-evident sealed packets, do not use any opened or torn packets.

Directions - Diphenhydramine

Do not use more than directed.

Adults and Children (12 Years and older) - take 1 to 2 caplets every 4 to 6 hours as needed. Do not take more than 12 caplets in 24 hours, or as directed by a doctor.

Do not give to children under 12 years of age.

Active Ingredients - After Cuts and Scrapes

Lidocaine Hydrochloride 2.5%

Benzalkonium Chloride .13%

Purpose - After Cuts and Scrapes

Anesthetic

Antiseptic

Uses - After Cuts and Scrapes

First aid for the temporary relief of pain and to protect from infection in minor cuts, scrapes and burns.

Warnings and Precautions - After Cuts and Scrapes

For External Use Only.

When using this product: do not get into eyes, do not use in large quantities, particularly over raw surfaces or blistered areas.

Stop use and ask a doctor if rash, redness or swelling occurs or pain increases. In case of deep puncture wounds, animal bites or serious burns consult a doctor.

If swallowed, get medical help or contact a poison control center right away.

If in eyes, flush with water for 15 minutes and call a doctor.

Keep out of Reach of Children.

Directions - After Cuts and Scrapes

Shake Well. Clean affected area. Spray on the area 1 to 3 times daily. Adults and children 2 years and older, apply to affected area. Children under 2 years, ask a doctor.

Active Ingredient - After Burn

Lidocaine Hydrochloride 2.5%

Purpose - After Burn

Topical Analgesic

Use - After Burn

For the temporary relief of pain due to minor burns, sunburn, minor cuts, scrapes or minor skin irritations

Warnings and Precautions - After Burn

For external use only.

When using this product: avoid contact with eyes, do not use in large quantities, particularly over raw surfaces or blistered areas, do not use longer than 1 week unless directed by a doctor, or in case of deep puncture wounds, animal bites or serious burns, consult a doctor.

Stop use and ask a doctor if conditions or symptoms persist for more than 7 days or clear up and occur again within a few days.

Keep out of Reach of Children.

If swallowed, get medical help or contact a poison control center right away.

If in eyes, flush with water for 15 minutes and call a doctor

Adults and Children 2 years and older, apply small amount to affected area, not more than 3 times daily.

Children under 2 years, consult a doctor.

Inactive Ingredients - After Burn

Aloe Vera Gel, Benzalkonium Chloride, Carbomer 980, glycerol, USP, herbal fragrance, menthol, polysorbate 20, Propylene glycol, purified water, sodium hydroxide (50%)